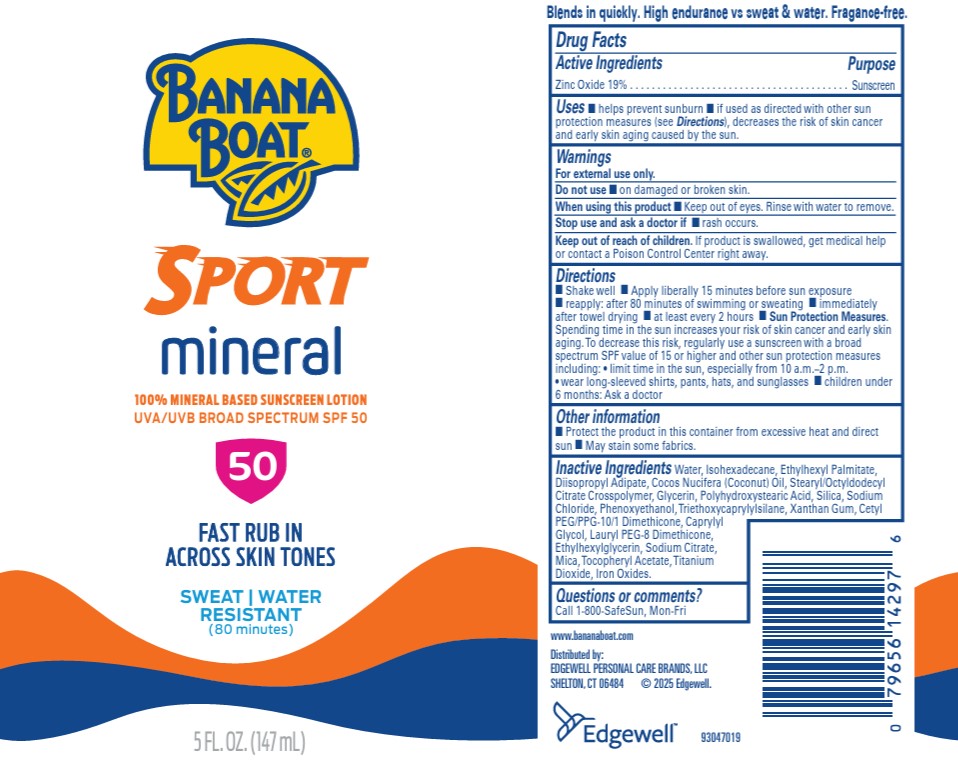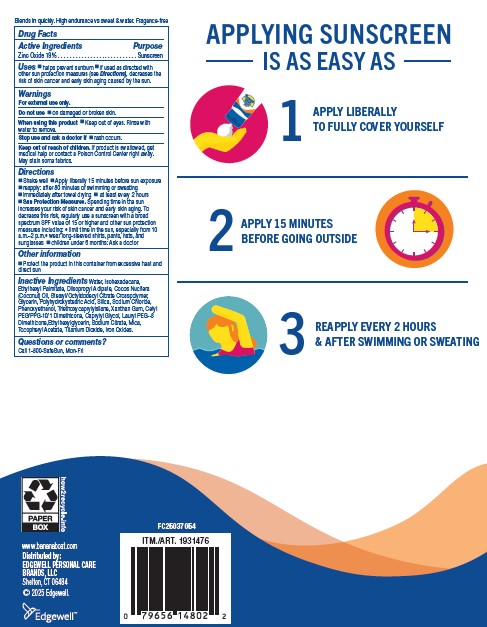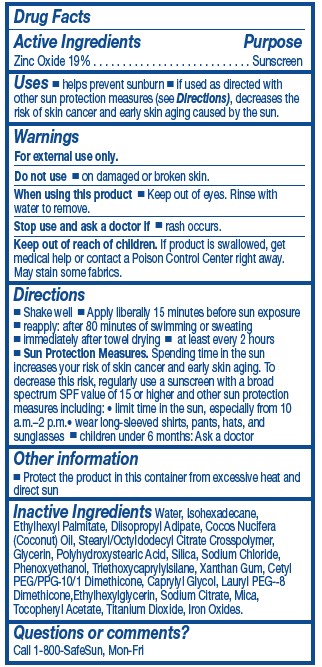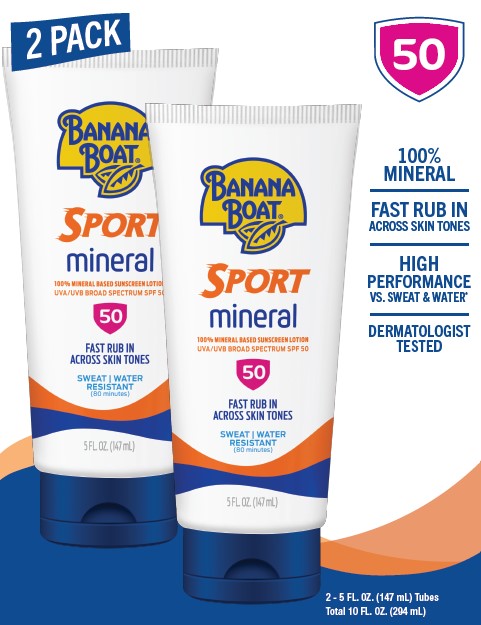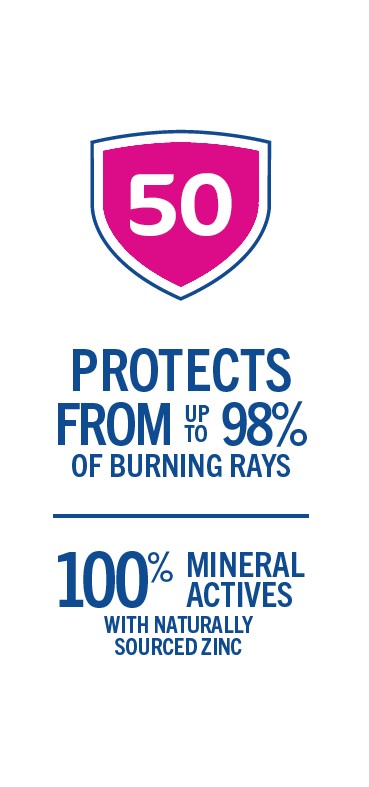 DRUG LABEL: Banana Boat
NDC: 63354-374 | Form: LOTION
Manufacturer: Edgewell Personal Care Brands LLC
Category: otc | Type: HUMAN OTC DRUG LABEL
Date: 20250923

ACTIVE INGREDIENTS: ZINC OXIDE 19 g/100 g
INACTIVE INGREDIENTS: ISOHEXADECANE; TRIETHOXYCAPRYLYLSILANE; CETYL PEG/PPG-10/1 DIMETHICONE (HLB 2); LAURYL PEG-8 DIMETHICONE (300 CPS); SODIUM CITRATE; POLYHYDROXYSTEARIC ACID (2300 MW); WATER; GLYCERIN; SILICON DIOXIDE; CAPRYLYL GLYCOL; ETHYLHEXYL PALMITATE; DIISOPROPYL ADIPATE; COCONUT OIL; STEARYL/OCTYLDODECYL CITRATE CROSSPOLYMER; MICA; FERRIC OXIDE YELLOW; TITANIUM DIOXIDE; PHENOXYETHANOL; XANTHAN GUM; ETHYLHEXYLGLYCERIN; SODIUM CHLORIDE; .ALPHA.-TOCOPHEROL ACETATE

Active Ingredients

Zinc Oxide 19%

Purpose

Sunscreen

Uses

- helps prevent sunburn. if used as directed with other sun protection measures (see Directions), decreases the risk of skin cancer and early skin aging caused by the sun.

Warnings

For external use only.

May stain some fabrics.

Do not use

on damaged or broken skin.

When using this product

• Keep out of eyes. Rinse with water to remove.

Stop use and ask a doctor

if rash occurs.

Keep out of reach of children

If product is swallowed, get medical help or contact a Poison Control Center right away.

Directions

• Shake well • Apply liberally 15 minutes before sun exposure • reapply: after 80 minutes of swimming or sweating • immediately after towel drying • at least every 2 hours • Sun Protection Measures.Spending time in the sun increases your risk of skin cancer and early skin aging. To decrease this risk, regularly use a sunscreen with a broad spectrum SPF value of 15 or higher and other sun protection measures including: • limit time in the sun, especially from 10 a.m.–2 p.m. • wear long-sleeved shirts, pants, hats, and sunglasses • children under 6 months: Ask a doctor

Other information

Protect the product in this container from excessive heat and direct sun

Inactive Ingredients

Water, Isohexadecane, Ethylhexyl Palmitate, Diisopropyl Adipate, Cocos Nucifera (Coconut) Oil, Stearyl/Octyldodecyl Citrate Crosspolymer, Glycerin, Polyhydroxystearic Acid, Silica, Sodium Chloride, Phenoxyethanol, Triethoxycaprylylsilane, Xanthan Gum, Cetyl PEG/PPG10/1 Dimethicone, Caprylyl Glycol, Lauryl PEG-8 Dimethicone, Ethylhexylglycerin, Sodium Citrate, Mica, Tocopheryl Acetate, Titanium Dioxide, Iron Oxides.

Questions or comments?

Call 1-800-SafeSun, Mon-Fri

Principal Display Panel

BANANA BOAT
SPORT
mineral
100% MINERAL BASED SUNSCREEN LOTION
UVA/UVB BROAD SPECTRUM, SPF 50
50
FAST RUB IN
ACROSS SKIN TONES
SWEAT | WATER
RESISTANT
(80 minutes)
5 FL. OZ. (147 mL)

BOTTLE
BANANA BOAT
SPORT
mineral
100% MINERAL BASED SUNSCREEN LOTION
UVA/UVB BROAD SPECTRUM, SPF 50
50
FAST RUB IN
ACROSS SKIN TONES
SWEAT | WATER
RESISTANT
(80 minutes)
5 FL. OZ. (147 mL)

Carton

50

PROTECTS UP TO 98%

OF BURNING RAYS

100% MINERAL ACTIVES

WITH NATURALLY

SOURCED ZINC

2 PACK

50

100%

MINERAL

FATS RUB IN

ACROSS SKIN TONES

HIGH

PERFORMANCE

VS. SWEAT & WATER

DERMATOLOGIST

TESTED

2 - 5 FL. OZ (147 mL) Tubes

Total 10 FL OZ.

(294 mL)